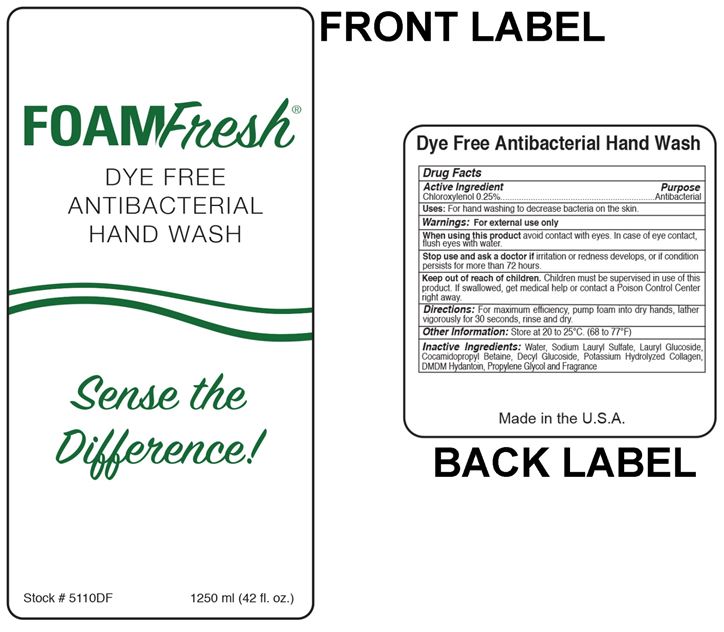 DRUG LABEL: FoamFresh Dye Free Antibacterial Hand Wash
NDC: 11429-1010 | Form: SOLUTION
Manufacturer: Woodbine Products Company
Category: otc | Type: HUMAN OTC DRUG LABEL
Date: 20241125

ACTIVE INGREDIENTS: CHLOROXYLENOL 2.5 mg/1 mL
INACTIVE INGREDIENTS: WATER; SODIUM LAURYL SULFATE; LAURYL GLUCOSIDE; COCAMIDOPROPYL BETAINE; DECYL GLUCOSIDE; DMDM HYDANTOIN; PROPYLENE GLYCOL

Drug Facts 11429-1010

Active Ingredient

Chloroxylenol 0.25%

Purpose

Antibacterial

Uses:

For hand washing to decrease bacteria on the skin.

Warnings:

For external use only

When using this product avoid contact with eyes.

In case of eye contact, flush eyes with water.

Stop use and ask a doctor if irritation or redness develops, or if condition persists for more than 72 hours.

Keep out of reach of children.

Children must be supervised in use of this product.

If swallowed, get medical help or contact a Poison Control Center right away.

Directions:

For maximum efficiency, pump foam into dry hands, lather vigorous for 30 seconds, rinse and dry.

Other Information:

Store at 20 to 25C.(68 to 77F)

Inactive Ingredients:

Water, Sodium Lauryl Sulfate, Lauryl Glucoside, Cocamidopropyl Betaine, Decyl Glucoside. Potassiom Hydrolyzed Collagen, DMDM Hydantoin, Propylene Glycol and Fragrance

PACKAGE LABEL

FOAMFresh

DYE FREE

ANTIBACTERIAL

Hand WASH

Sense the

Difference

Stock # 5110DF

1250 ml (42 fl.oz.)